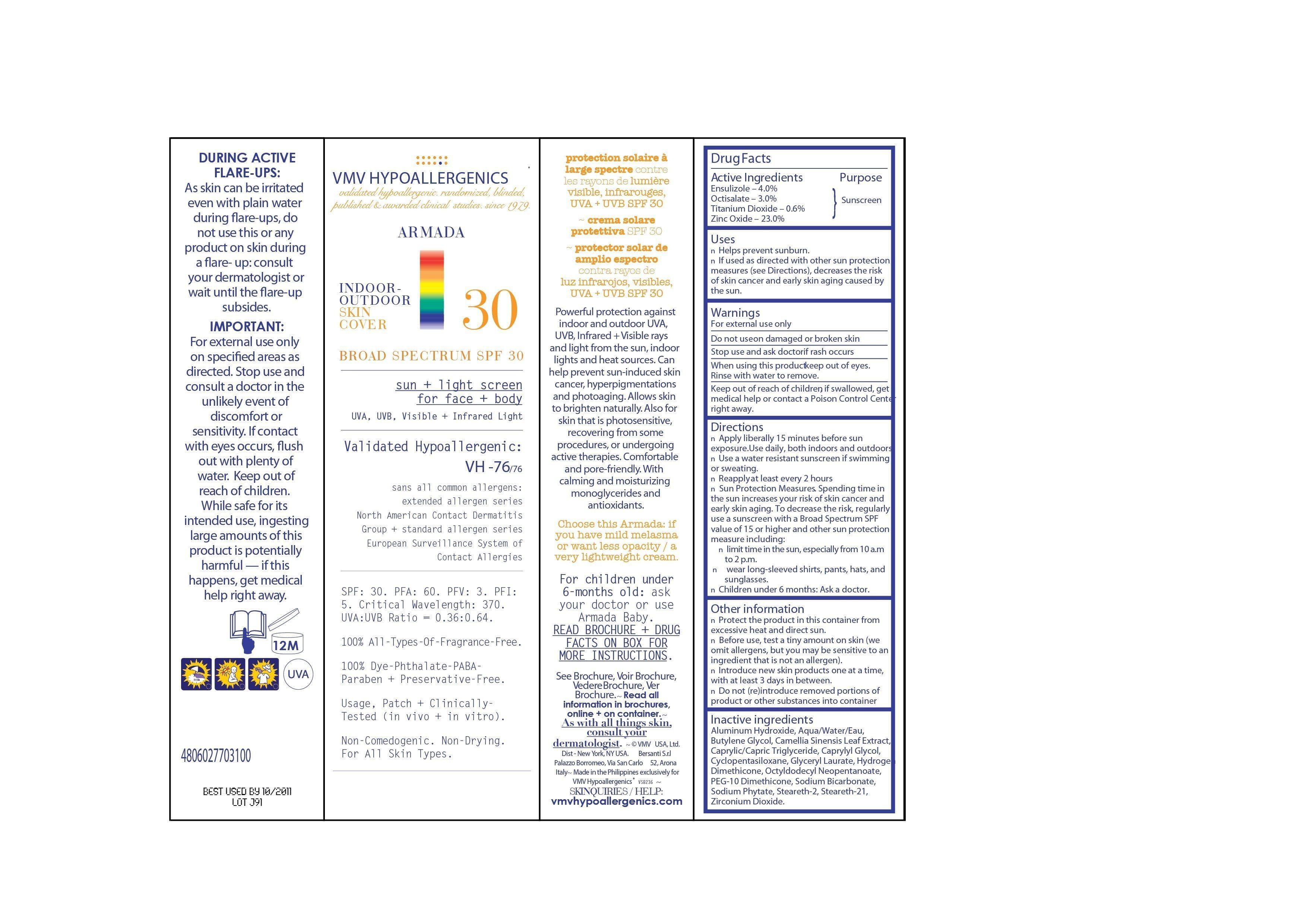 DRUG LABEL: VMV HYPOALLERGENICS ARMADA 30
NDC: 69774-536 | Form: CREAM
Manufacturer: SKIN SCIENCES LABORATORY INC.
Category: otc | Type: HUMAN OTC DRUG LABEL
Date: 20150430

ACTIVE INGREDIENTS: TITANIUM DIOXIDE 0.6 g/85 g; OCTISALATE 3 g/85 g; ENSULIZOLE 4 g/85 g; ZINC OXIDE 23 g/85 g
INACTIVE INGREDIENTS: WATER

Uses

• Helps prevent sunburn
• If used as directed with other sun protection measures (see Direction), decrease the risk of skin cancer and early skin aging caused by the sun.

Warnings

For external use only
Do not use on damaged skin or broken skin
Stop use and ask doctor if rash occurs
When using this product keep out of eyes. Rinse with water to remove.
Keep out of reach of children, if swallowed, get medical help or contact a Poison Control Center right away.

Directions

• Apply liberally 15 minutes before sun exposure. Use daily, both indoors and outdoors.
• Use water resistant sunscreen if swimming or sweating.
• Reapply at least every 2 hours.
• Sun Protection Measures. Spending time in the sun increases your risk of skin cancer and early skin aging. To decrease the risk, regularly use a sunscreen with a Broad Spectrum SPF value of 15 or higher and other sun protection measuring including:
• Limit time in the sun, especially from 10a.m. to 2 p.m.
• Wear long-sleeved shirt, pants, hats and sunglasses.
• Children under 6 months: Ask a doctor.

Other Informations

• Protect the product in this container from excessive heat and direct sun.
• Before use, test a tiny amount on skin (we omit allergens, but you may be sensitive to an ingredient that is not an allergen).
• Introduce new skin products one at a time, with at least 3 days in between.
• Do not (re) introduce removed portions od product or other substances into container

Inactive INgredients

Aluminum Hydroxide, Aqua/Water/Eau, Butylene Glycol, Camellia Sinensis Leaf Extract, Caprylic/Capric Triglyceride, Caprylyl Glycol, Cyclopentasiloxane, Glyceryl Laurate, Hydrogen Dimethicone, Octyldodecyl Neopentanoate, PEG-10 Dimethicone, Sodium Bicarbonate, Sodium Phytate, Steareth-2, Steareth-21, Zirconium Dioxide.

Principal Display Panel

VMV HYPOALLERGENICS

validated hypoallergenic. randomized, blinded,

published & awarded clinical studies, since 1979.

ARMADA 30

INDOOR-

OUTDOOR

SKIN

COVER

BROAD SPECTRUM SPF 30

sun + light screen

for face + body

UVA, UVB, Visible + Infrared Light

Validated Hypoallergenic:

VH -76/76

sans all common allergens:

extended allergen series

North American Contact Dermatitis

Group + Standard allergen series

European Survellance System of

Contact Allergies

SPF: 30. PFA: 60. PFV: 3. PFI:

5. Critical Wavelength: 370.

UVA:UVB Ratio = 0.36:0.64.

100% All-Types-Of-Fragrance-Free.

100% Dye-Phthalate-PABA-

Paraben + Preservative-Free.

Usage, Patch + Clinically-

Tested (in vivo + in vitro).

Non-Comedogenic. Non-Drying.

For All Skin Types.

85g (3.0 Oz.) - 85g e

Active Ingredient

Ensulizole

Octisalate

Titanium Dioxide

Zinc Oxide

Active Ingredient

Ensulizole - 4.0%

Octisalate - 3.0%

Titanium Dioxide - 0.6%

Zinc Oxide - 23.0%